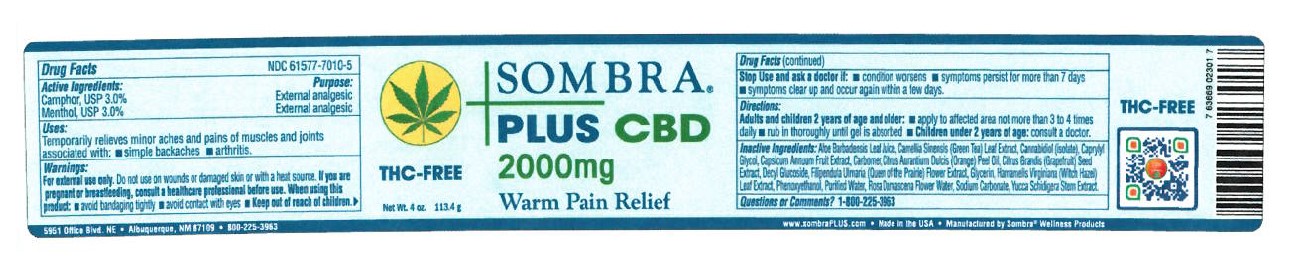 DRUG LABEL: Sombra Plus CBD 2000mg Warm Theapy
NDC: 61577-7120 | Form: GEL
Manufacturer: Sombra Cosmetics INC
Category: otc | Type: HUMAN OTC DRUG LABEL
Date: 20220524

ACTIVE INGREDIENTS: MENTHOL 0.03 g/1 g; CAMPHOR (SYNTHETIC) 0.03 g/1 g
INACTIVE INGREDIENTS: ALOE VERA LEAF; DECYL GLUCOSIDE; WATER; CAPSAICIN; GRAPEFRUIT SEED OIL; GREEN TEA LEAF; FILIPENDULA ULMARIA FLOWER; ROSA CENTIFOLIA FLOWER OIL; SODIUM CARBONATE; GLYCERIN; WITCH HAZEL; YUCCA SCHIDIGERA ROOT; ORANGE PEEL; PHENOXYETHANOL; CAPRYLYL GLYCOL; CANNABIDIOL

Sombra Plus 2000mg CBD Warm Therapy

Active Ingredients

Menthol USP 3%, Camphor USP 3%

Purpose

External Analgesic

Keep out of reach of children

Uses

Temporarily relieves minor aches and pains of muscles and joints associated with: arthritis, simple backaches

Warnings

For external use only. Do not use on wounds or damaged skin. When using this product: avoid bandaging tightly, avoid contact with eyes, keep out of reach of children.

Stop use and ask doctor if: condition worsens, symptoms persist for more than 7 days, clear up and occur again within a few days.

Directions

adults and children 2 years of age and older: apply to affected area not more than 3 to 4 times daily, rub in thoroughly until gel is absorbed, children under 2 years of age: consult a doctor.

Inactive Ingredients

Aloe Baradensis Leaf Juice, Camillia Sinensis (Green Tea) Leaf Extract, Cannabidiol (isolate), Caprylyl Glycol, Capsicum Annuum Fruit Extract, Carbomer, Citrus Aurantium Dulcis (Orange) Peel Oil, Citrus Grandis (Grapefruit) Seed Extract, Decyl Glucoside, Glycerin, Hamamelis Viginiana (Witch Hazel) Leaf Extract, Phenoxyethanol, Purified Water, Rose Damascena Flower Water, Sodium Carbonate, Filipendula Ulmaris (Queen of the Prairie) Flower Extract, Yucca Schidigera Root Extract.